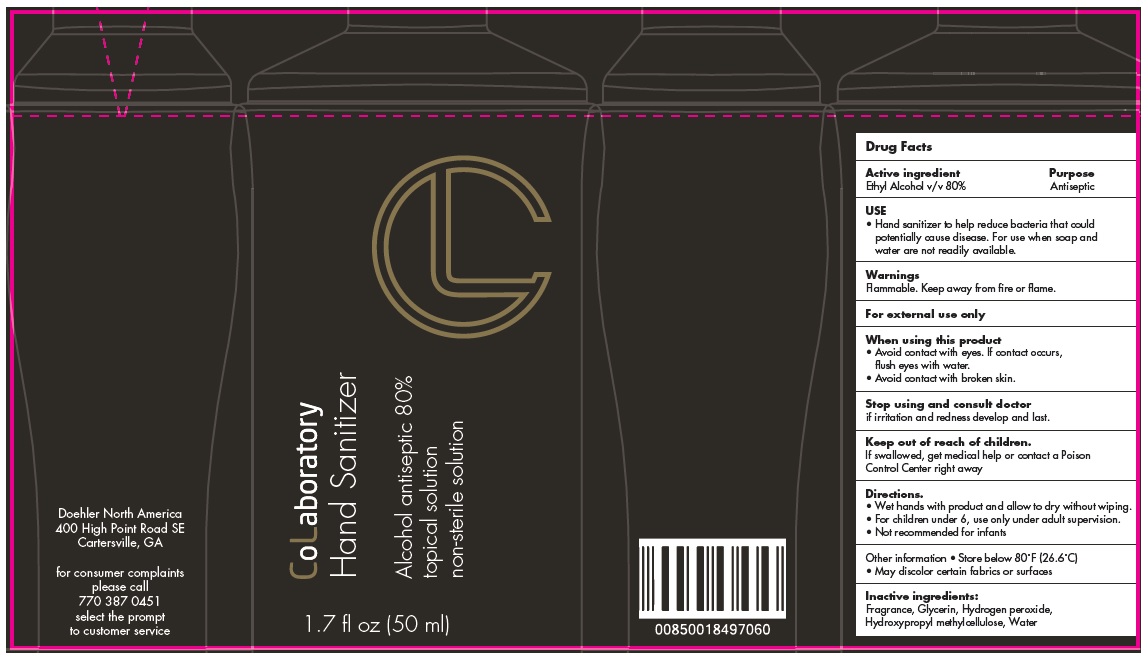 DRUG LABEL: CoLaboratory Hand Sanitizer
NDC: 77278-002 | Form: GEL
Manufacturer: Doehler USA Inc.
Category: otc | Type: HUMAN OTC DRUG LABEL
Date: 20200818

ACTIVE INGREDIENTS: ALCOHOL 80 mL/100 mL
INACTIVE INGREDIENTS: GLYCERIN; HYDROGEN PEROXIDE; HYPROMELLOSE, UNSPECIFIED; WATER

CoLaboratory Hand Sanitizer

Active ingredient

Ethyl Alcohol v/v 80%

Purpose

Antiseptic

USE

• Hand sanitizer to help reduce bacteria that could potentially cause disease. For use when soap and water are not readily available.

Warnings

Flammable. Keep away from fire or flame.

For external use only

When using this product
• Avoid contact with eyes. If contact occurs, flush eyes with water.
• Avoid contact with broken skin.

Stop using and consult doctor
if irritation or redness develop and last.

Keep out of reach of children.
If swallowed, get medical help or contact a Poison Control Center right away

Directions.

• Wet hands with product & allow to dry without wiping
• For children under 6, use only under adult supervision.
• Not recommended for infants

Other information

• Store below 80°F (26.6°C)
• May discolor certain fabrics or surfaces

Inactive ingredients:

Fragrance, Glycerin, Hydrogen peroxide, Hydroxypropyl methylcellulose, Water

Alcohol antiseptic 80%

topical solution

non-sterile solution

Doehler North America
400 High Point Road SE
Cartersville, GA

for consumer complaints please call 770 387 0451
select the prompt to customer service